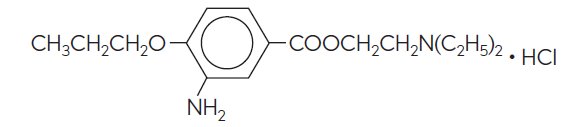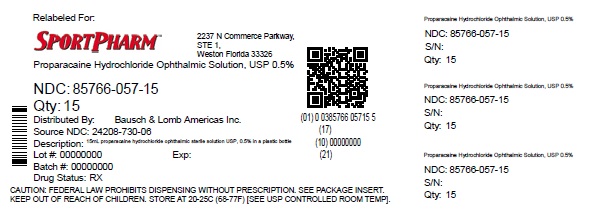 DRUG LABEL: Proparacaine Hydrochloride
NDC: 85766-057 | Form: SOLUTION/ DROPS
Manufacturer: Sportpharm, Inc. dba Sportpharm
Category: prescription | Type: HUMAN PRESCRIPTION DRUG LABEL
Date: 20250822

ACTIVE INGREDIENTS: PROPARACAINE HYDROCHLORIDE 5 mg/1 mL
INACTIVE INGREDIENTS: BENZALKONIUM CHLORIDE; GLYCERIN; HYDROCHLORIC ACID; WATER; SODIUM HYDROXIDE

DESCRIPTION

Proparacaine hydrochloride ophthalmic solution USP, 0.5% is a topical local anesthetic for ophthalmic use. The active ingredient is represented by the structural formula:

Established name:
Proparacaine Hydrochloride

Chemical name:
Benzoic acid, 3-amino-4-propoxy-,2-(diethylamino) ethyl ester, monohydrochloride

Molecular weight: 330.86

Each mL contains:

Active:proparacaine hydrochloride 5 mg (0.5%). Inactives:glycerin and purified water. The pH may be adjusted with hydrochloric acid and/or sodium hydroxide. Preservative:benzalkonium chloride (0.01%).

CLINICAL PHARMACOLOGY

Proparacaine hydrochloride ophthalmic solution is a rapidly-acting topical anesthetic, with induced anesthesia lasting approximately 10-20 minutes.

INDICATIONS AND USAGE

Proparacaine hydrochloride ophthalmic solution is indicated for procedures in which a topical ophthalmic anesthetic is indicated; corneal anesthesia of short duration, e.g. tonometry, gonioscopy, removal of corneal foreign bodies and for short corneal and conjunctival procedures.

CONTRAINDICATIONS

Proparacaine hydrochloride ophthalmic solution is contraindicated in patients with known hypersensitivity to any of the ingredients of this preparation.

WARNINGS

NOT FOR INJECTION INTO THE EYE - FOR TOPICAL OPHTHALMIC USE ONLY

Prolonged use of a topical ocular anesthetic is not recommended. It may produce permanent corneal opacification with accompanying visual loss.

PRECAUTIONS

Carcinogenesis, Mutagenesis, Impairment of Fertility

Long-term studies in animals have not been performed to evaluate carcinogenic potential, mutagenicity or possible impairment of fertility in males or females.

Pregnancy

Animal reproduction studies have not been conducted with proparacaine hydrochloride ophthalmic solution USP, 0.5%. It is also not known whether proparacaine hydrochloride can cause fetal harm when administered to a pregnant woman or can affect reproduction capacity. Proparacaine hydrochloride should be administered to a pregnant woman only if clearly needed.

Nursing Mothers

It is not known whether this drug is excreted in human milk. Because many drugs are excreted in human milk, caution should be exercised when proparacaine hydrochloride is administered to a nursing woman.

Pediatric Use

Safety and effectiveness of proparacaine hydrochloride ophthalmic solution in pediatric patients have been established. Use of proparacaine hydrochloride is supported by evidence from adequate and well-controlled studies in adults and children over the age of twelve, and safety information in neonates and other pediatric patients.

Geriatric Use

No overall clinical differences in safety of effectiveness have been observed between the elderly and other adult patients.

ADVERSE REACTIONS

Occasional temporary stinging, burning and conjunctival redness may occur with the use of proparacaine. A rare, severe, immediate-type, apparently hyperallergic corneal reaction characterized by acute, intense and diffuse epithelial keratitis, a gray, ground glass appearance, sloughing of large areas of necrotic epithelium, corneal filaments and sometimes iritis with descemetitis has been reported.

Allergic contact dermatitis from proparacaine with drying and fissuring of the fingertips has been reported.

To report SUSPECTED ADVERSE REACTIONS, contact Bausch & Lomb Incorporated at 1-800-553-5340 or FDA at 1-800-FDA-1088 or www.fda.gov/medwatch.

DOSAGE AND ADMINISTRATION

Usual Dosage: Removal of foreign bodies and sutures, and for tonometry: 1 to 2 drops (in single instillations) in each eye before operating.

Short corneal and conjunctival procedures: 1 drop in each eye every 5 to 10 minutes for 5 to 7 doses.

NOTE:Proparacaine hydrochloride ophthalmic solution USP, 0.5% should be clear, colorless to faint yellow color. If the solution becomes darker, discard the solution.

FOR TOPICAL OPHTHALMIC USE ONLY

HOW SUPPLIED

Proparacaine hydrochloride ophthalmic solution USP, 0.5% is supplied in a plastic bottle with a controlled drop tip and a white polypropylene cap in the following size:

NDC 85766-057-15 15 mL bottle (relabeled from NDC 24208-730-06)

Storage:

Refrigerate at 2°C to 8°C (36°F to 46°F). Protect from light. Keep tightly closed.

DO NOT USE IF IMPRINTED NECKBAND IS NOT INTACT.

Keep out of reach of children.

Distributed by:

Sportpharm

2237 N Commerce Parkway,

STE 1, Weston, Florida-33326

Relabeled by:

Enovachem PHARMACEUTICALS

Torrance, CA 90501